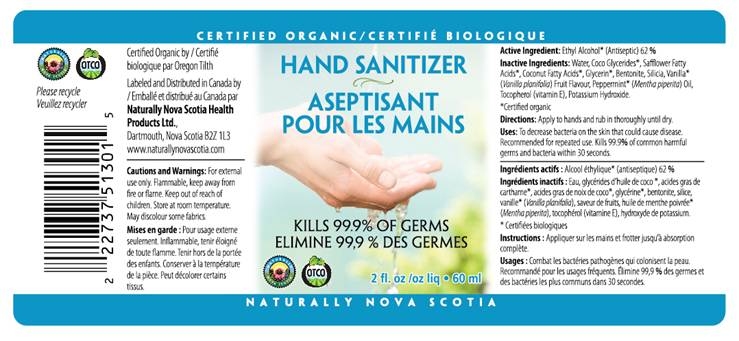 DRUG LABEL: Naturally Nova Scotia Hand Sanitizer
NDC: 59958-100 | Form: GEL
Manufacturer: Owen Biosciences, Inc.
Category: otc | Type: HUMAN OTC DRUG LABEL
Date: 20091208

ACTIVE INGREDIENTS: Alcohol 62.0 g/100 g

Drug Facts

ACTIVE INGREDIENT: Ethyl Alcohol* (Antiseptic) 62%

USES:

To decrease bacteria on the skin that could cause disease.
Recommended for repeated use. Kills 99.9% of common harmful
germs and bacteria within 30 seconds.

Cautions and Warnings:

For external use only. Flammable, keep away from
fire or flame. Keep out of reach of
children. Store at 20 to 25ºC. May
discolor some fabrics.

DIRECTIONS:

Apply to hands and rub in thoroughly until dry.

INACTIVE INGREDIENTS:

Water, Coco Glycerides*, Safflower Fatty
Acids*, Coconut Fatty Acids*, Glycerin*, Bentonite, Silicia, Vanilla*
(Vanilla planifolia) Fruit Flavour, Peppermint* (Mentha piperita) Oil,
Tocopherol (vitamin E), Potasium Hydroxide.
*Certified organic